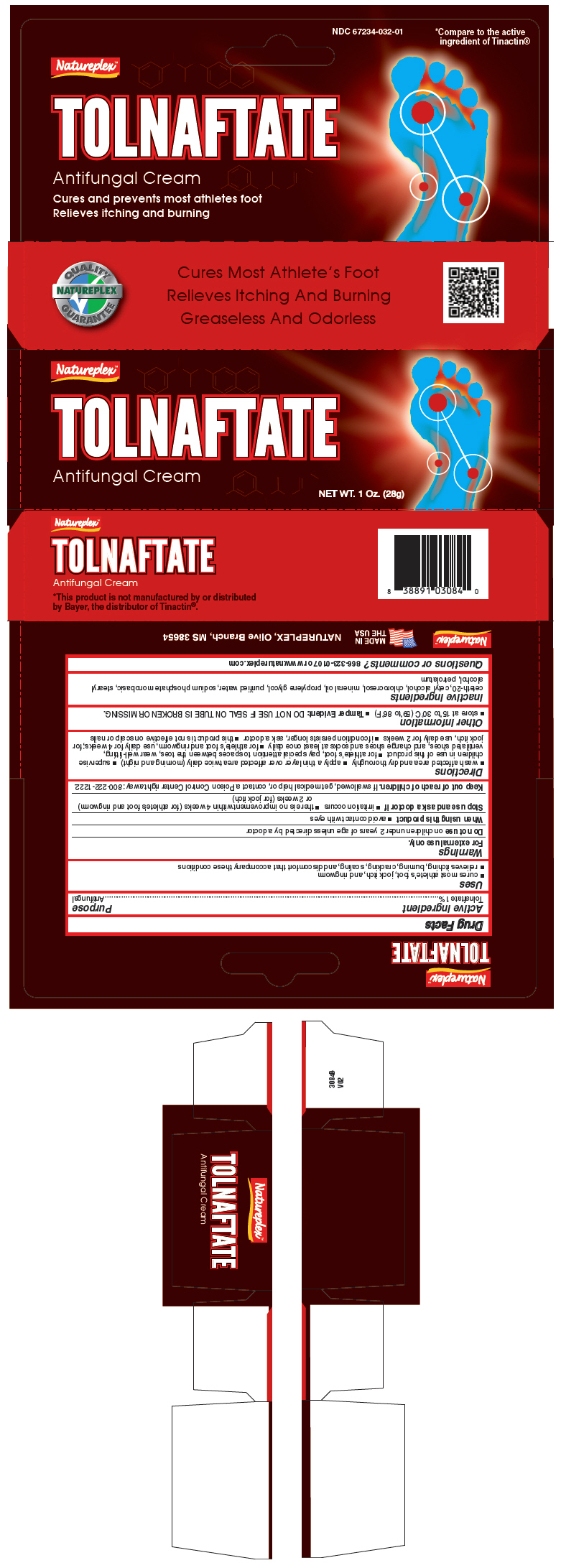 DRUG LABEL: NATUREPLEX TOLNAFTATE 
NDC: 67234-032 | Form: CREAM
Manufacturer: Natureplex, LLC
Category: otc | Type: HUMAN OTC DRUG LABEL
Date: 20250115

ACTIVE INGREDIENTS: TOLNAFTATE 10 mg/1 g
INACTIVE INGREDIENTS: CETETH-20; CETYL ALCOHOL; CHLOROCRESOL; MINERAL OIL; SODIUM PHOSPHATE, MONOBASIC, UNSPECIFIED FORM; PROPYLENE GLYCOL; WATER; STEARYL ALCOHOL; PETROLATUM

NATUREPLEX™ TOLNAFTATE
ANTIFUNGAL CREAM

Drug Facts

Active ingredient

Tolnaftate 1%

Purpose

Antifungal

Uses

- cures most athlete's foot, jock itch, and ringworm
- relieves itching, burning, cracking, scaling, and discomfort that accompany these conditions

Warnings

For external use only.

Do not use on children under 2 years of age unless directed by a doctor

When using this product

- avoid contact with eyes

Stop use and ask a doctor if

- irritation occurs
- there is no improvement within 4 weeks (for athlete's foot and ringworm) or 2 weeks (for jock itch)

Keep out of reach of children. If swallowed, get medical help or, contact a Poison Control Center right away: 800-222-1222.

Directions

- wash affected area and dry thoroughly
- apply a thin layer over affected area twice daily (morning and night)
- supervise children in use of this product
- for athlete's foot, pay special attention to spaces between the toes, wear well-fitting, ventilated shoes, and change shoes and socks at least once daily
- for athlete's foot and ringworm, use daily for 4 weeks; for jock itch, use daily for 2 weeks
- if condition persists longer, ask a doctor
- this product is not effective on scalp or nails

Other information

- store at 15°to 30°C (59°to 86°F)
- Tamper Evident: DO NOT USE IF SEAL ON TUBE IS BROKEN OR MISSING.

Inactive ingredients

ceteth-20, cetyl alcohol, chlorocresol, mineral oil, propylene glycol, purified water, sodium phosphate monobasic, stearyl alcohol, petrolatum

Questions or comments?

866-323-0107 or www.natureplex.com

PRINCIPAL DISPLAY PANEL - 28 g Tube Carton

Natureplex™

TOLNAFTATE

Antifungal Cream

NET WT. 1 Oz. (28g)